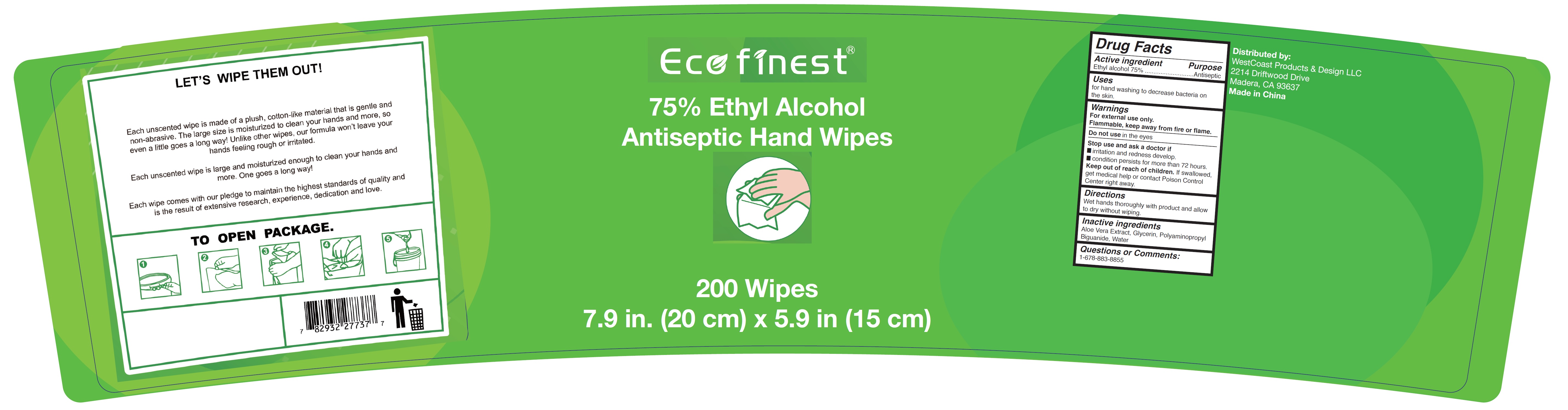 DRUG LABEL: Antiseptic Hand Wipes
NDC: 80385-000 | Form: CLOTH
Manufacturer: WestCoast Products & Design LLC
Category: otc | Type: HUMAN OTC DRUG LABEL
Date: 20200915

ACTIVE INGREDIENTS: ALCOHOL 0.75 mL/1 mL
INACTIVE INGREDIENTS: ALOE VERA LEAF; GLYCERIN; POLYAMINOPROPYL BIGUANIDE; WATER

Antiseptic Hand Wipes

Active ingredient

Ethyl alcohol 75%

Purpose

Antiseptic

Uses

for hand washing to decrease bacteria on the skin.

Warnings

For external use only.
Flammable, keep away from fire or flame.

Do not use

in the eyes

Stop use and ask a doctor if

- irritation and redness develop.
- condition persists for more than 72 hours.

Keep out of reach of children.

If swallowed, get medical help or contact Poison Control Center right away.

Directions

Wet hands thoroughly with product and allow to dry without wiping.

Inactive ingredients

Aloe Vera Extract, Glycerin, Polyaminopropyl Biguanide, Water

Questions or Comments:

1-678-883-8855